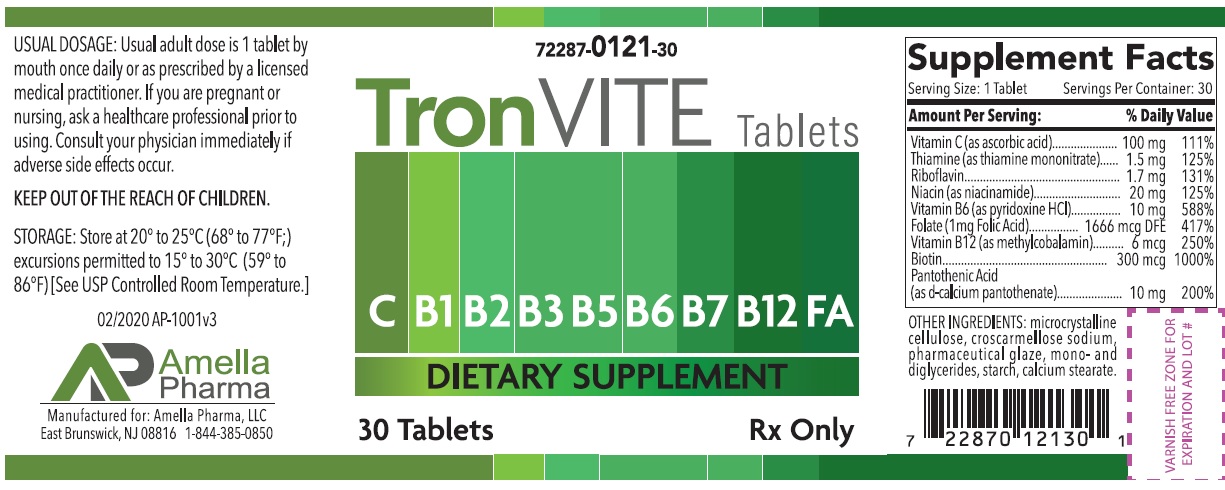 DRUG LABEL: TRONVite
NDC: 72287-121 | Form: TABLET, COATED
Manufacturer: AMELLA PHARMA, LLC
Category: other | Type: DIETARY SUPPLEMENT
Date: 20200915

ACTIVE INGREDIENTS: ASCORBIC ACID 100 mg/1 1; THIAMINE MONONITRATE 1.5 mg/1 1; RIBOFLAVIN 1.7 mg/1 1; NIACINAMIDE 20 mg/1 1; PYRIDOXINE HYDROCHLORIDE 10 mg/1 1; FOLIC ACID 1 mg/1 1; METHYLCOBALAMIN 6 ug/1 1; BIOTIN 300 ug/1 1; PANTOTHENIC ACID 10 mg/1 1
INACTIVE INGREDIENTS: MICROCRYSTALLINE CELLULOSE; CROSCARMELLOSE SODIUM; SHELLAC; GLYCERYL MONOSTEARATE; STARCH, CORN; CALCIUM STEARATE

TRONVite

TRONVITE Tablets Dietary Supplement Dispensed by Prescription†

Supplement Facts Serving Size: 1 Tablet Serving Per Container: 30
Amount Per Serving |  | % Daily Value
Vitamin C (as ascorbic Acid) | 100 mg | 111%
Thiamine (as thiamine mononitrate) | 1.5 mg | 125%
Riboflavin | 1.7 mg | 131%
Niacin (as niacinamide) | 20 mg | 125%
Vitamin B6 (as pyridoxine HCl) | 10 mg | 588%
Folic Acid (1mg Folic Acid) | 1 mg | 417%
Vitamin B12 (as methylcobalamin) | 6 mcg | 250%
Biotin | 300 mcg | 1000%
Pantothenic Acid (as d-calcium pantothenate) | 10 mg | 200%

OTHER INGREDIENTS: microcrystalline cellulose, croscarmellose sodium, pharmaceutical glaze, mono- and diglycerides, starch, calcium stearate.

DESCRIPTION

TRONVITE Tablets is an orally administered prescription vitamin formulation for the clinical dietary management of suboptimal nutritional status in patients where advanced folate supplementation is required and nutritional supplementation in physiologically stressful conditions for maintenance of good health is needed.

TRONVITE is a small, round, yellow, clear-coated tablet, with debossed "A" on one side.

PRECAUTIONS

CONTRAINDICATIONS
This product is contraindicated in patients with known hypersensitivity to any of the ingredients.

PRECAUTIONS
This product is contraindicated in patients with a known hypersensitivity to any of the ingredients.

TRONVITE Tablets should only be used under the direction and supervision of a licensed medical practitioner. Use with caution in patients that may have a medical condition, are pregnant, lactating, trying to conceive, under the age of 18, or taking medications.

Folic acid supplementation may obscure pernicious anemia, in that hematologic remission can occur while neurological manifestations progress.

WARNINGS

KEEP OUT OF THE REACH OF CHILDREN.

Pregnancy and Lactation:
TRONVITE Tablets is not intended for use in pregnant or lactating patients

ADVERSE REACTIONS
Allergic sensitizations have been reported following oral administration of folic acid. Consult your physician immediately if adverse side effects occur.

DOSAGE AND ADMINISTRATION

Usual adult dose is 1 tablet by mouth once or twice daily or as prescribed by a licensed medical practitioner.

HOW SUPPLIED HEALTH CLAIM:

TRONVITE Tablets are supplied as a small, round, yellow, clear-coated tablet, with debossed "A" on one side. TronVite Tablets is available as the following:
72287-121-30* 30ct bottle

Store at 20° to 25°C (68° to 77°F; excursions permitted to 15° to 30°C (59° to 86°F) [See USP Controlled Room Temperature]

Manufactured for:
Amella Pharma, LLC
E Brunswick, NJ 08816

Call your doctor for medical advice about side effects. You may report side effects to Amella Pharma, LLC at 1-844-385-0850.

Issued: 09/2018 AP1002v2

*Amella Pharma does not represent these product codes to be National Drug Codes (NDC). Product codes are formatted according to standard industry practice, to meet the formatting requirement by pedigree reporting and supply-chain control including pharmacies.

† This product is a prescription-folate with or without other dietary ingredients that – due to increased folate levels increased risk associated with masking of B12 deficiency (pernicious anemia) requires administration under the care of a licensed medical practitioner (61 FR 8760). The most appropriate way to ensure pedigree reporting consistent with these regulatory guidelines and safety monitoring is to dispense this product only by prescription (Rx). This is not an Orange Book product. This product may be administered only under a physician’s supervision and all prescriptions using this product shall be pursuant to state statutes as applicable. The ingredients, indication or claims of this product are not to be construed to be drug claims.